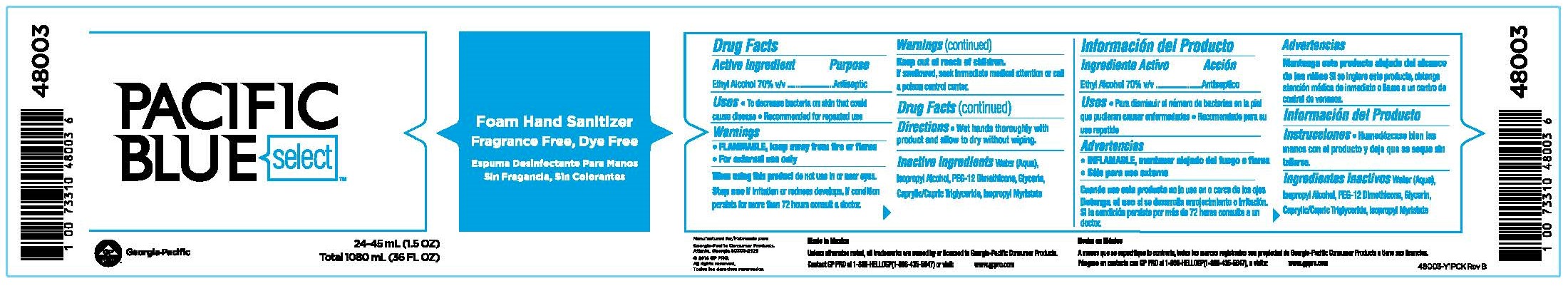 DRUG LABEL: Pacific Blue Select Foam Hand Sanitizer, Fragrance Free, Dye Free
NDC: 54622-311 | Form: LIQUID
Manufacturer: Georgia-Pacific Consumer Products
Category: otc | Type: HUMAN OTC DRUG LABEL
Date: 20240502

ACTIVE INGREDIENTS: ALCOHOL 70 mL/100 mL
INACTIVE INGREDIENTS: WATER; ISOPROPYL ALCOHOL; PEG-12 DIMETHICONE; GLYCERIN; MEDIUM-CHAIN TRIGLYCERIDES; ISOPROPYL MYRISTATE

54622-311

Drug Facts

Active ingredient

Ethyl alcohol, 70% v/v

Purpose

Antiseptic

Uses

- To decrease bacteria on skin that could cause disease
- Recommended for repeated use

Warnings

- FLAMMABLE, keep away from fire or flame
- For external use only

When using this product

Do not use in or near eyes.

Stop use

if irritation or redness develops. If condition persists for more than 72 hours consult a doctor.

Keep out of reach of children.

If swallowed, seek immediate medical attention or call a poison control center.

Directions

Wet hands thoroughly with product and allow to dry without wiping.

Inactive ingredients

Water (Aqua), Isopropyl Alcohol, PEG-12 Dimethicone, Glycerin, Caprylic/Capric Triglyceride, Isopropyl Myristate

PACKAGE LABEL

Pacific Blue Select™
Foam Hand Sanitizer
Fragrance and Dye Free
24-45mL (1.5 FL OZ)

Total 1080mL (36 FL OZ)
Georgia-Pacific Consumer Products
Atlanta, GA 30303-2529
Made in Mexico
©2018 GP PRO.
All rights reserved.
Unless otherwise noted, all trademarks are owned by
or licensed to Georgia-Pacific Consumer Products.

Contact GP PRO at 1-866-HELLOGP (1-866-435-5647) or visit

www.gppro.com